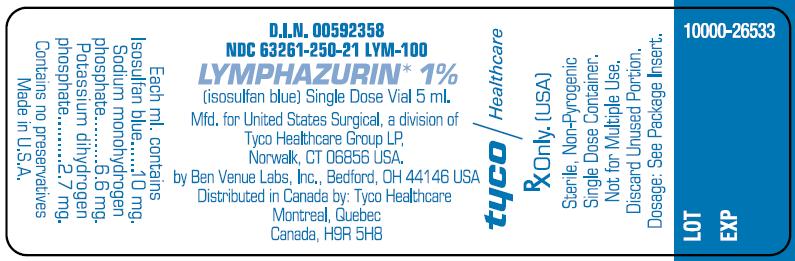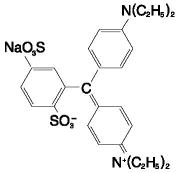 DRUG LABEL: LYMPHAZURIN
NDC: 63261-250 | Form: INJECTION, SOLUTION
Manufacturer: UNITED STATES SURGICAL CORPORATION
Category: prescription | Type: HUMAN PRESCRIPTION DRUG LABEL
Date: 20120131

ACTIVE INGREDIENTS: ISOSULFAN BLUE 10 mg/1 mL
INACTIVE INGREDIENTS: SODIUM PHOSPHATE, DIBASIC, ANHYDROUS; POTASSIUM PHOSPHATE, MONOBASIC; WATER

HIGHLIGHTS OF PRESCRIBING INFORMATION

These highlights do not include all the information needed to use LYMPHAZURIN safely and effectively. See full prescribing information for LYMPHAZURIN.
LYMPHAZURIN injection, solution for subcutaneous use
Initial U.S. Approval: 1981

RECENT MAJOR CHANGES

Warnings and Precautions, Interference with Oxygen Saturation and Methemoglobin Measurements (5.3). 10/2007

1 INDICATIONS AND USAGE

Lymphazurin™ 1% (isosulfan blue) upon subcutaneous administration, delineates the lymphatic vessels draining the region of injection. It is an adjunct to lymphography in: primary and secondary lymphedema of the extremities; chyluria, chylous ascites or chylothorax; lymph node involvement by primary or secondary neoplasm; lymph node response to therapeutic modalities (1.1).

2 DOSAGE AND ADMINISTRATION

Lymphazurin™ 1% is to be administered subcutaneously, one-half (1/2) ml into three (3) interdigital spaces of each extremity per study. A maximum dose of 3 ml (30 mg) isosulfan blue is, therefore, injected (2.1).

3 DOSAGE FORMS AND STRENGTHS

1% aqueous solution (isosulfan blue)

4 CONTRAINDICATIONS

Hypersensitivity to triphenylmethane or related compounds (4).

5 WARNINGS AND PRECAUTIONS

- Life-threatening anaphylactic reactions have occurred after Lymphazurin 1% administration. Monitor patients closely for at least 60 minutes after administration of Lymphazurin 1% (5.1).
- The admixture of Lymphazurin 1% with local anesthetics results in an immediate precipitation of 4-9% drug complex. Use a separate syringe for anesthetics (5.2).
- Lymphazurin 1% interferes with measurements in peripheral blood pulse oximetry. Arterial blood gas analysis may be needed (5.3).

6 ADVERSE REACTIONS

Hypersensitivity reactions: Hypersensitivity reactions occurring approximately 2% of patients and include life-threatening anaphylactic reactions with respiratory distress, shock, angioedema, urticaria, pruritus. A death has been reported following IV administration of a similar compound (6).
To report SUSPECTED ADVERSE REACTIONS, contact U.S. Surgical at 1-800-522-0263 option 5 and website or FDA at 1-800-FDA-1088 or www.fda.gov/medwatch

7 DRUG INTERACTIONS

No drug interactions have been identified for Lymphazurin 1% (7).

8 USE IN SPECIFIC POPULATIONS

- Caution should be exercised when Lymphazurin 1% is administered to nursing mothers (8.3).
- Safety and effectiveness of Lymphazurin 1% in children has not been established (8.4).

FULL PRESCRIBING INFORMATION

1 INDICATIONS AND USAGE

1.1 Lymphatic Vessel Delineation

Lymphazuirn™ 1% (isosulfan blue) upon subcutaneous administration, delineates lymphatic vessels draining the region of injection. It is an adjunct to lymphography in: primary and secondary lymphedema of the extremities; chyluria, chylous ascites or chylothorax; lymph node involvement by primary or secondary neoplasm; and lymph node response to therapeutic modalities.

2 DOSAGE AND ADMINISTRATION

2.1 Subcutaneous administration

Lymphazurin™ 1% is to be administered subcutaneously, one-half (1/2) ml into three (3) interdigital spaces of each extremity per study. A maximum dose of 3 ml (30 mg) isosulfan blue is, therefore, injected.

3 DOSAGE FORMS AND STRENGTHS

1% aqueous solution (isosulfan blue)

4 CONTRAINDICATIONS

Lymphazurin™ 1% (isosulfan blue) is contraindicated in those individuals with known hypersensitivity to triphenylmethane or related compounds.

5 WARNINGS AND PRECAUTIONS

5.1 Hypersensitivity Reactions

Life-threatening anaphylactic reactions (respiratory distress, shock, angioedema) have occurred after Lymphazurin 1% administration. Reactions are more likely to occur in patients with a history of bronchial asthma, allergies, drug reactions or previous reactions to triphenylmethane dyes. Monitor patients closely for at least 60 minutes after administration of Lymphazurin 1%. Trained personnel should be available to administer emergency care including resuscitation.

5.2 Precipitation of Lymphazurin 1% by Lidocaine

The admixture of Lymphazurin 1% (with local anesthetics (i.e. lidocaine)) in the same syringe results in an immediate precipitation of 4 – 9% drug complex. Use a separate syringe to administer a local anesthetic.

5.3 Interference with Oxygen Saturation and Methemoglobin Measurements

Lymphazurin 1% interferes with measurements of oxygen saturation in peripheral blood by pulse oximetry and can cause falsely low readings. The interference effect is maximal at 30 minutes and minimal generally by four hours after administration. Arterial blood gas analysis may be needed to verify decreased arterial partial pressure of oxygen.
Lymphazurin 1% may also cause falsely elevated readings of methemoglobin by arterial blood gas analyzer. Therefore, co-oximetry may be needed to verify methemoglobin level.

6 ADVERSE REACTIONS

6.1 Postmarketing Experience

Hypersensitivity Reactions: Case series report an overall incidence of hypersensitivity reactions in approximately 2% of patients. Life-threatening anaphylactic reactions have occurred. Manifestations include respiratory distress, shock, angioedema, urticaria, pruritus. A death has been reported following administration of a similar compound employed to estimate the depth of a severe burn. Reactions are more likely to occur in patients with a personal or family history of bronchial asthma, significant allergies, drug reactions or previous reactions to triphenylmethane dyes [see Warnings and Precautions (5)].
Laboratory tests: Lymphazurin 1% interferes with measurements of oxygen saturation by pulse oximetry and of methemoglobin by gas analyzer [see Warnings and Precautions (5)].
Skin: transient or long-term (tattooing) blue coloration.

7 DRUG INTERACTIONS

No Drug Interactions have been identified with Lymphazurin 1%.

8 USE IN SPECIFIC POPULATIONS

8.3 Nursing Mothers

It is not known whether this drug is excreted in human milk. Because many drugs are excreted in human milk, caution should be exercised when Lymphazurin™ 1% (isosulfan blue) is administered to a nursing mother.

8.4 Pediatric Use

Safety and effectiveness of Lymphazurin™ 1% (isosulfan blue) in children have not been established.

10 OVERDOSAGE

Do not exceed indicated recommended dosage as overdosage levels have not been identified for Lymphazurin 1%.

11 DESCRIPTION

The chemical name of Lymphazurin 1% (isosulfan blue) is N-[4-[[4-(diethylamino)phenyl] (2,5-disulfophenyl) methylene]-2,5-cyclohexadien-1-ylidene]-N-ethylehananamunium hydroxide, inner salt, sodium salt. Its structural formula is:

Lymphazurin 1% is a sterile aqueous solution for subcutaneous administration. Phosphate buffer in sterile, pyrogen free water is added in sufficient quantity to yield a final pH of 6.8-7.4. Each ml of solution contains 10 mg Isosulfan blue, 6.6 mg sodium monohydrogen phosphate and 2.7 mg potassium dihydrogen phosphate. The solution contains no preservative. Lymphazurin 1% is a contrast agent for the delineation of lymphatic vessels.

12 CLINICAL PHARMACOLOGY

12.2 Pharmacodynamics

Following subcutaneous administration, Lymphazurin 1% binds to serum proteins and is picked up by the lymphatic vessels. Thus, the lymphatic vessels are delineated by the blue dye.

12.3 Pharmacokinetics

Up to 10% of the subcutaneously administered dose of Lymphazurin 1% is excreted unchanged in the urine in 24 hours in human.

13 NONCLINICAL TOXICOLOGY

13.1 Carcinogenesis, Mutagenesis, Impairment of Fertility

Long-term studies in animals have not been performed to evaluate the carcinogenic potential of Lymphazurin 1%. Reproduction studies in animals have not been conducted and, therefore, it is unknown if a problem concerning mutagenesis or impairment of fertility in either males or females exists.

13.2 Teratogenic Effects

Pregnancy Category C. Animal reproduction studies have not been conducted with Lymphazurin 1%. It is not known whether Lymphazurin 1% can cause fetal harm when administered to a pregnant woman or can affect reproduction capacity. Lymphazurin 1% should be given to a pregnant woman only if clearly needed.

16 HOW SUPPLIED/STORAGE AND HANDLING

Lymphazurin 1% is supplied as a 5 ml single dose vial, 1% aqueous solution in a phosphate buffer prepared by appropriate manufacturing to be sterile and pyrogen-free.

17 PATIENT COUNSELING INFORMATION

Inform patients that urine color may be blue for 24 hours following administration of Lymphazurin 1%.

PRINCIPAL DISPLAY PANEL

D.I.N. 00592358
NDC 63261-250-21 LYM-100
LYMPHAZURIN* 1%
(isosulfan blue) Single Dose Vial 5 ml.

Mfd. for United States Surgical, a division of
Tyco Healthcare Group LP,
Norwalk, CT 06856 USA.

by Ben Venue Labs, Inc., Bedford, OH 44146 USA

Distributed in Canada by: Tyco Healthcare
Montreal, Quebec
Canada, H9R 5H8